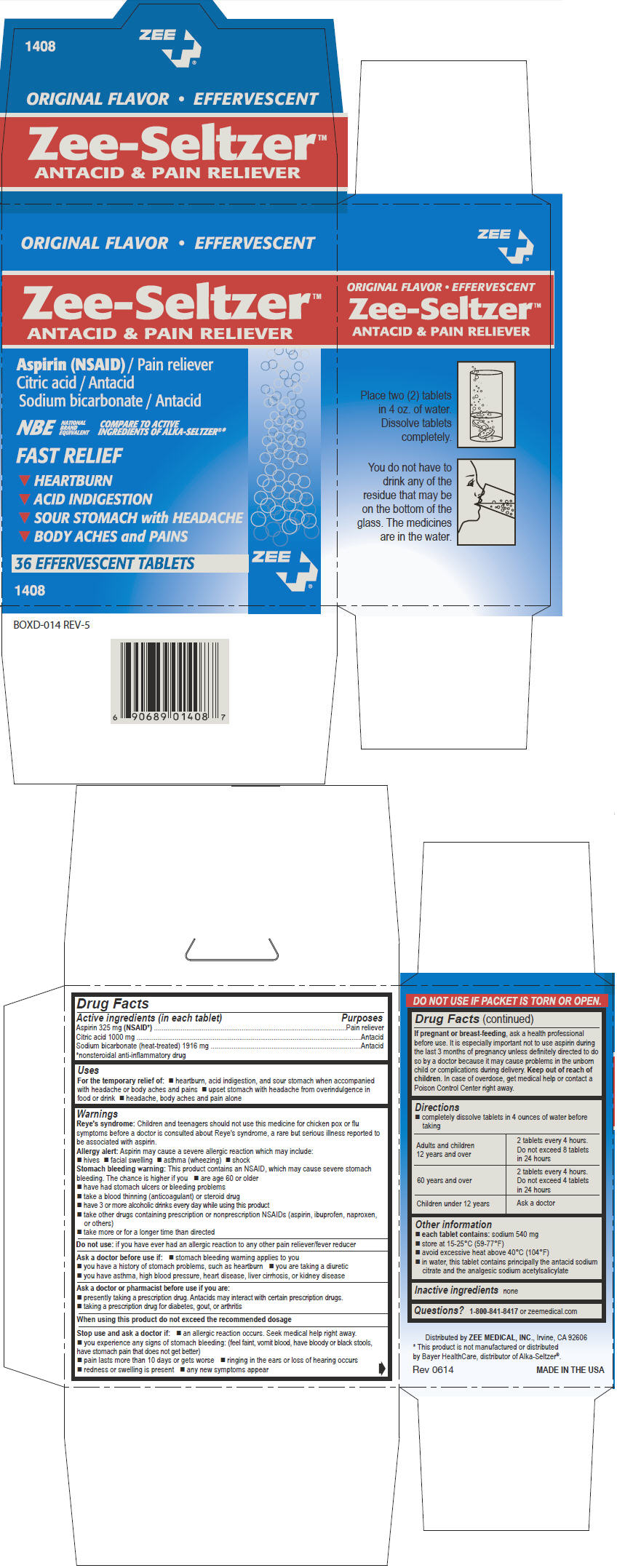 DRUG LABEL: Zee-Seltzer Antacid and Pain Reliever
NDC: 35418-233 | Form: TABLET, EFFERVESCENT
Manufacturer: ZEE MEDICAL
Category: otc | Type: HUMAN OTC DRUG LABEL
Date: 20141001

ACTIVE INGREDIENTS: Aspirin 325 mg/1 1; Citric Acid Monohydrate 1000 mg/1 1; Sodium Bicarbonate 1916 mg/1 1

Zee-Seltzer™ Antacid and Pain Reliever

Drug Facts

ACTIVE INGREDIENT

PURPOSE

Active ingredients (in each tablet) | Purposes
Aspirin 325 mg (NSAID [nonsteroidal anti-inflammatory drug]) | Pain reliever
Citric acid 1000 mg | Antacid
Sodium bicarbonate (heat-treated) 1916 mg | Antacid

Uses

For the temporary relief of:

- heartburn, acid indigestion, and sour stomach when accompanied with headache or body aches and pains
- upset stomach with headache from overindulgence in food or drink
- headache, body aches and pain alone

Warnings

Reye's syndrome

Children and teenagers should not use this medicine for chicken pox or flu symptoms before a doctor is consulted about Reye's syndrome, a rare but serious illness reported to be associated with aspirin.

Allergy alert

Aspirin may cause a severe allergic reaction which may include:

- hives
- facial swelling
- asthma (wheezing)
- shock

Stomach bleeding warning

This product contains an NSAID, which may cause severe stomach bleeding. The chance is higher if you

- are age 60 or older
- have had stomach ulcers or bleeding problems
- take a blood thinning (anticoagulant) or steroid drug
- have 3 or more alcoholic drinks every day while using this product
- take other drugs containing prescription or nonprescription NSAIDs (aspirin, ibuprofen, naproxen, or others)
- take more or for a longer time than directed

Do not use: if you have ever had an allergic reaction to any other pain reliever/fever reducer

Ask a doctor before use if

- stomach bleeding warning applies to you
- you have a history of stomach problems, such as heartburn
- you are taking a diuretic
- you have asthma, high blood pressure, heart disease, liver cirrhosis, or kidney disease

Ask a doctor or pharmacist before use if you are

- presently taking a prescription drug. Antacids may interact with certain prescription drugs.
- taking a prescription drug for diabetes, gout, or arthritis

Stop use and ask a doctor if

- an allergic reaction occurs. Seek medical help right away.
- you experience any signs of stomach bleeding: (feel faint, vomit blood, have bloody or black stools, have stomach pain that does not get better)
- pain lasts more than 10 days or gets worse
- ringing in the ears or loss of hearing occurs
- redness or swelling is present
- any new symptoms appear

PREGNANCY OR BREAST FEEDING

If pregnant or breast-feeding, ask a health professional before use. It is especially important not to use aspirin during the last 3 months of pregnancy unless definitely directed to do so by a doctor because it may cause problems in the unborn child or complications during delivery.

Keep out of reach of children. In case of overdose, get medical help or contact a Poison Control Center right away.

Directions

- completely dissolve tablets in 4 ounces of water before taking

Adults and children 12 years and over | 2 tablets every 4 hours. Do not exceed 8 tablets in 24 hours
60 years and over | 2 tablets every 4 hours. Do not exceed 4 tablets in 24 hours
Children under 12 years | Ask a doctor

Other information

- each tablet contains: sodium 540 mg
- store at 15-25°C (59-77°F)
- avoid excessive heat above 40°C (104°F)
- in water, this tablet contains principally the antacid sodium citrate and the analgesic sodium acetylsalicylate

Inactive ingredients

none

Questions?

1-800-841-8417 or zeemedical.com

Distributed by ZEE MEDICAL, INC., Irvine, CA 92606

PRINCIPAL DISPLAY PANEL - 36 Tablet Carton

ORIGINAL FLAVOR • EFFERVESCENT

Zee-Seltzer™
ANTACID & PAIN RELIEVER

Aspirin (NSAID) / Pain reliever
Citric acid / Antacid
Sodium bicarbonate / Antacid

NBE
NATIONAL
BRAND
EQUIVALENT
COMPARE TO ACTIVE
INGREDIENTS OF ALKA-SELTZER®*

FAST RELIEF

▼ HEARTBURN
▼ ACID INDIGESTION
▼ SOUR STOMACH with HEADACHE
▼ BODY ACHES and PAINS

36 EFFERVESCENT TABLETS

ZEE

1408